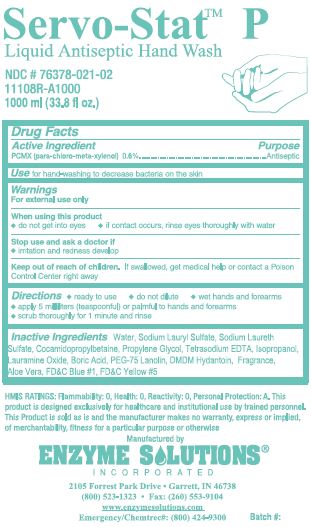 DRUG LABEL: Servo-Stat P Antiseptic Hand Wash
NDC: 76378-021 | Form: LIQUID
Manufacturer: Enzyme Solutions, Inc.
Category: otc | Type: HUMAN OTC DRUG LABEL
Date: 20250710

ACTIVE INGREDIENTS: CHLOROXYLENOL 0.6 g/100 mL
INACTIVE INGREDIENTS: WATER; SODIUM LAURYL SULFATE; SODIUM LAURETH-3 SULFATE; COCAMIDOPROPYL BETAINE; PROPYLENE GLYCOL; EDETATE SODIUM; ISOPROPYL ALCOHOL; LAURAMINE OXIDE; BORIC ACID; PEG-75 LANOLIN; DMDM HYDANTOIN; ALOE VERA LEAF; FD&C BLUE NO. 1; FD&C YELLOW NO. 5

Drug Facts 76378-021

Active Ingredient

PCMX (para-chloro-meta-xylenol) 0.6%

Purpose

Antiseptic

Use

for hand-washing to decrease bacteria on the skin

Warnings

For external use only

When using this product

do not get into eyes

if contact occurs, rinse eyes thoroughly with water

Stop use and ask a doctor if

irritation and redness develop

Keep out of reach of children.

If swallowed, get medical help or contact a Poison Control Center right away

Directions

ready to use

do not dilute

wet hands and forearms

apply 5 milliliters (teaspoonful) or palmful to hands and forearms

scrub thoroughly for 1 minute and rinse

Inactive Ingredients

Water, Sodium Lauryl Sulfate, Sodium Laureth Sulfate, Cocamidopropylbetaine, Propylene Glycol, Tetrasodium EDTA, Isopropanol, Lauramine Oxide, Boric Acid, PEG-75 Lanolin, DMDM Hydantoin, Fragrance, Aloe Vera, FDC Blue #1, FDC Yellow #5

PACKAGE LABEL

Servo-Stat P

Liquid Antiseptic Hand Wash

NDC # 76378-021-02

11108R-A1000

1000 ml (33.8 fl oz.)